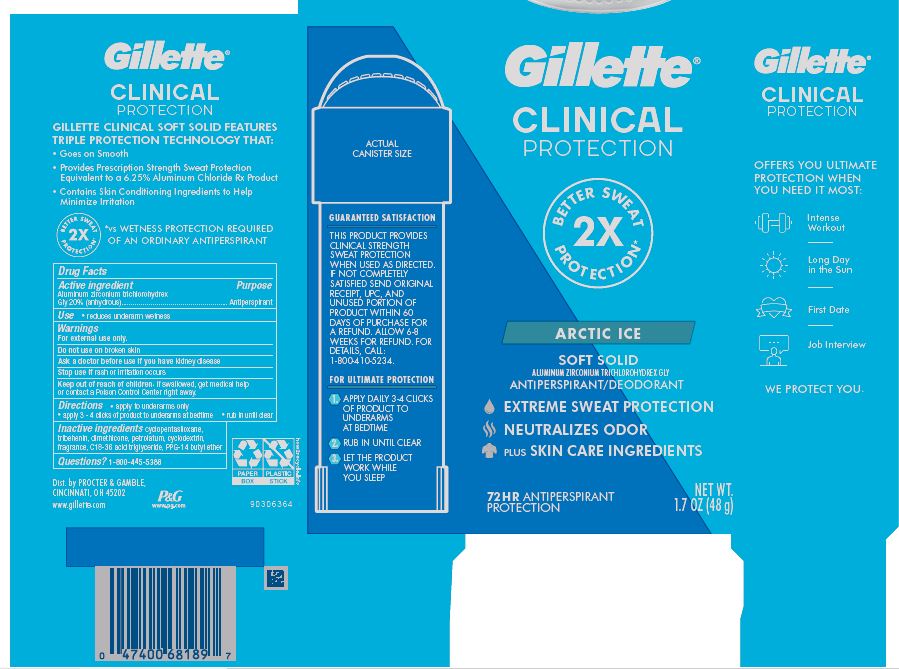 DRUG LABEL: Gillette Clinical Protection Arctic Ice Soft
NDC: 84126-019 | Form: CREAM
Manufacturer: The Procter & Gamble Manufacturing Company
Category: otc | Type: HUMAN OTC DRUG LABEL
Date: 20251231

ACTIVE INGREDIENTS: ALUMINUM ZIRCONIUM TRICHLOROHYDREX GLY 20 g/100 g
INACTIVE INGREDIENTS: BETADEX; C18-36 ACID TRIGLYCERIDE; CYCLOMETHICONE 5; DIMETHICONE; PETROLATUM; TRIBEHENIN; PPG-14 BUTYL ETHER

Gillette® Clinical Protection Arctic Ice Soft Solid

Drug Facts

Active ingredient

Aluminum zirconium trichlorohydrex Gly 20% (anhydrous)

Purpose

Antiperspirant

Use

- reduces underarm wetness
- extra effective

Warnings

For external use only.

Do not use on broken skin

Ask a doctor before use if you have kidney disease

Stop use if rash or irritation occurs

Keep out of reach of children. If swallowed, get medical help or contact a Poison Control Center right away.

Directions

- apply to underarms only
- apply 3 clicks of product to underarms at bedtime
- rub in until clear

Inactive ingredients

cyclopentasiloxane, tribehenin, dimethicone, petrolatum, cyclodextrin, fragrance, C18-36 acid triglyceride, PPG-14 butyl ether

Questions?

1-800-445-5388

Dist. by PROCTER & GAMBLE,
CINCINNATI, OH 45202.

PRINCIPAL DISPLAY PANEL - 45 g Cylinder Carton

Gillette®
CLINICAL PROTECTION

ARCTIC ICE

SOFT SOLID

ALUMINUM ZIRCONIUM TRICHLOROHYDREX GLY

ANTIPERSPIRANT/DEODORANT

NET WT. 1.7 OZ (45 g)